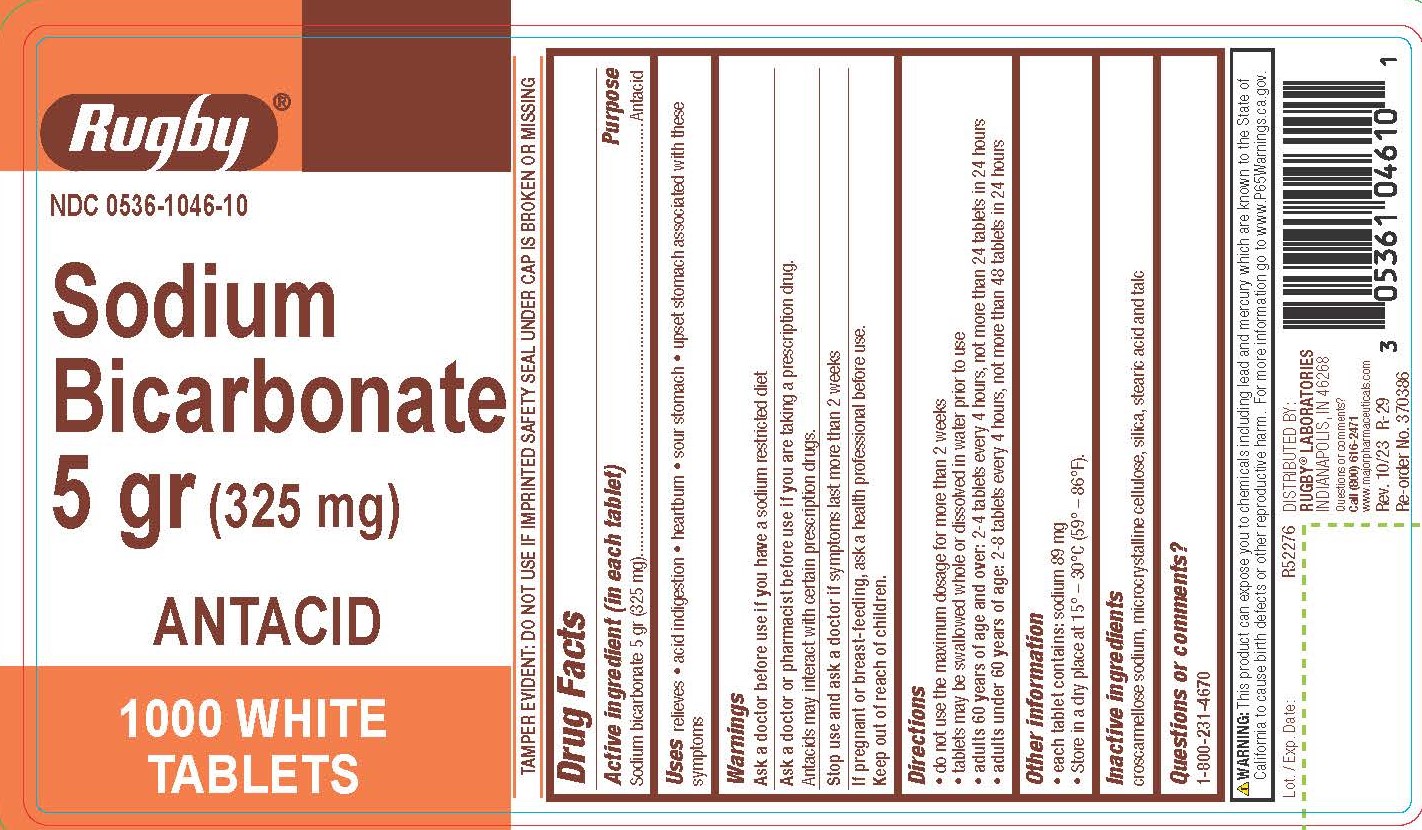 DRUG LABEL: Sodium Bicarbonate Antacid
NDC: 0536-1046 | Form: TABLET
Manufacturer: Rugby Laboratories
Category: otc | Type: HUMAN OTC DRUG LABEL
Date: 20231206

ACTIVE INGREDIENTS: SODIUM BICARBONATE 325 mg/1 1
INACTIVE INGREDIENTS: CROSCARMELLOSE SODIUM; CELLULOSE, MICROCRYSTALLINE; STEARIC ACID; SILICON DIOXIDE; TALC

4621 - Rugby

Drug Facts

Active ingredient (in each tablet)

Sodium bicarbonate 5 gr (325 mg)

Purpose

Antacid

Uses

relieves

- acid indigestion
- heartburn
- sour stomach
- upset stomach associated with these symptoms

Warnings

Ask a doctor before use if you have a sodium restricted diet

Ask a doctor or pharmacist before use if you are taking a prescription drug.

Antacids may interact with certain prescription drugs.

Stop use and ask a doctor if symptoms last more than 2 weeks

PREGNANCY OR BREAST FEEDING

If pregnant or breast-feeding, ask a health professional before use.

Keep out of reach of children.

Directions

- do not use the maximum dosage for more than 2 weeks
- tablets may be swallowed whole or dissolved in water prior to use
- adults 60 years of age and over: 2-4 tablets every 4 hours, not more than 24 tablets in 24 hours
- adults under 60 years of age: 2-8 tablets every 4 hours, not more than 48 tablets in 24 hours

Other information

- each tablet contains: sodium 89 mg
- Store in a dry place at 15º - 30ºC (59º - 86º F)

Inactive ingredients

croscarmellose sodium, microcrystalline cellulose, silica, stearic acid, and talc

Questions or comments?

1-800-231-4670

TAMPER EVIDENT: DO NOT USE IF IMPRINTED SAFETY SEAL UNDER CAP IS BROKEN OR MISSING

WARNING: This product can expose you to chemicals including lead and mercury which are known to the State of
California to cause birth defects or other reproductive harm. For more information go to www.P65Warnings.ca.gov.

DISTRIBUTED BY:

RUGBY® LABORATORIES

INDIANAPOLIS, IN 46268

Questions or comments?

Call (800) 616-2471

www.majorpharmaceuticals.com

Rev. 10/23 R-29

PACKAGE LABEL

Rugby

NDC 0536-1046-10

Sodium Bicarbonate 5 gr (325 mg)

ANTACID

1000 WHITE TABLETS